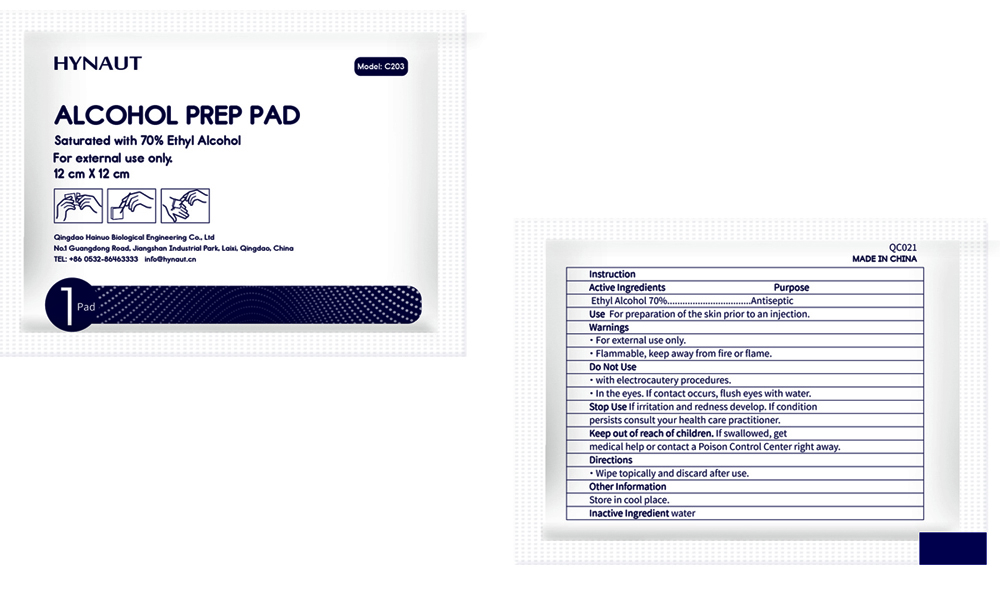 DRUG LABEL: Hynaut Alcohol Prep Pad
NDC: 78149-002 | Form: CLOTH
Manufacturer: Qingdao Hainuo Biological Engineering Co., Ltd.
Category: otc | Type: HUMAN OTC DRUG LABEL
Date: 20250306

ACTIVE INGREDIENTS: ALCOHOL 70 mL/100 g
INACTIVE INGREDIENTS: WATER

ACTIVE INGREDIENT

Alcohol 70%......................Antiseptic

PURPOSE

Antiseptic

Use

For preparation of the skin prior to an injection

Warnings

- For external use only.
- Flammable, keep away from fire or flame.

Do not use

- with electrocautery procedures.
- in the eyes. If contact occurs, flush eyes with water.

Stop use

if irritation and redness develop.If condition persists consult your health care parctitioner.

Keep out of reach of children. If swallowed, get medical help or contact a Poison Control Center right away

Directions

Wipe topically and discard after use.

Other information

Store in cool place

INACTIVE INGREDIENT

Water

PACKAGE LABEL

78149-002-01